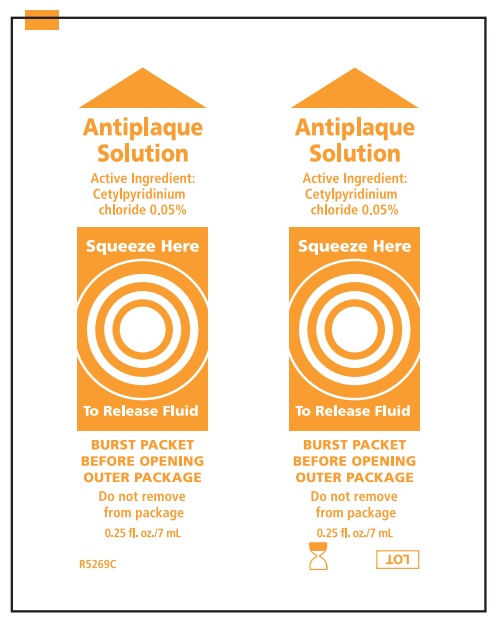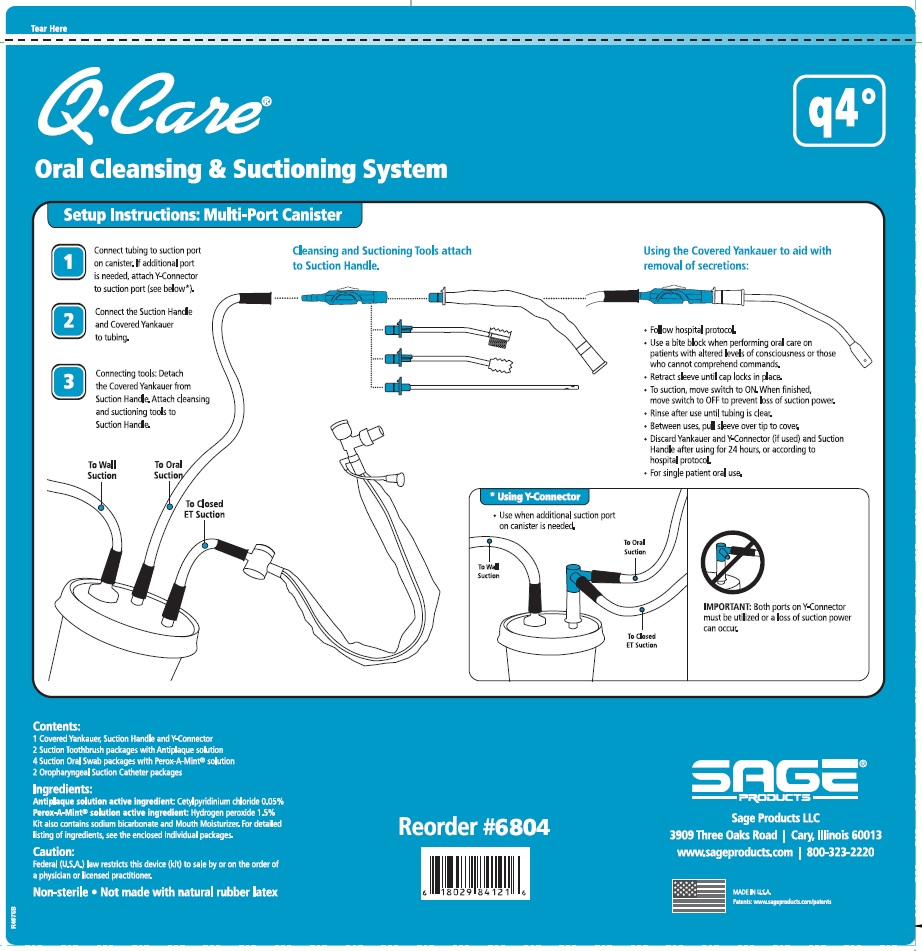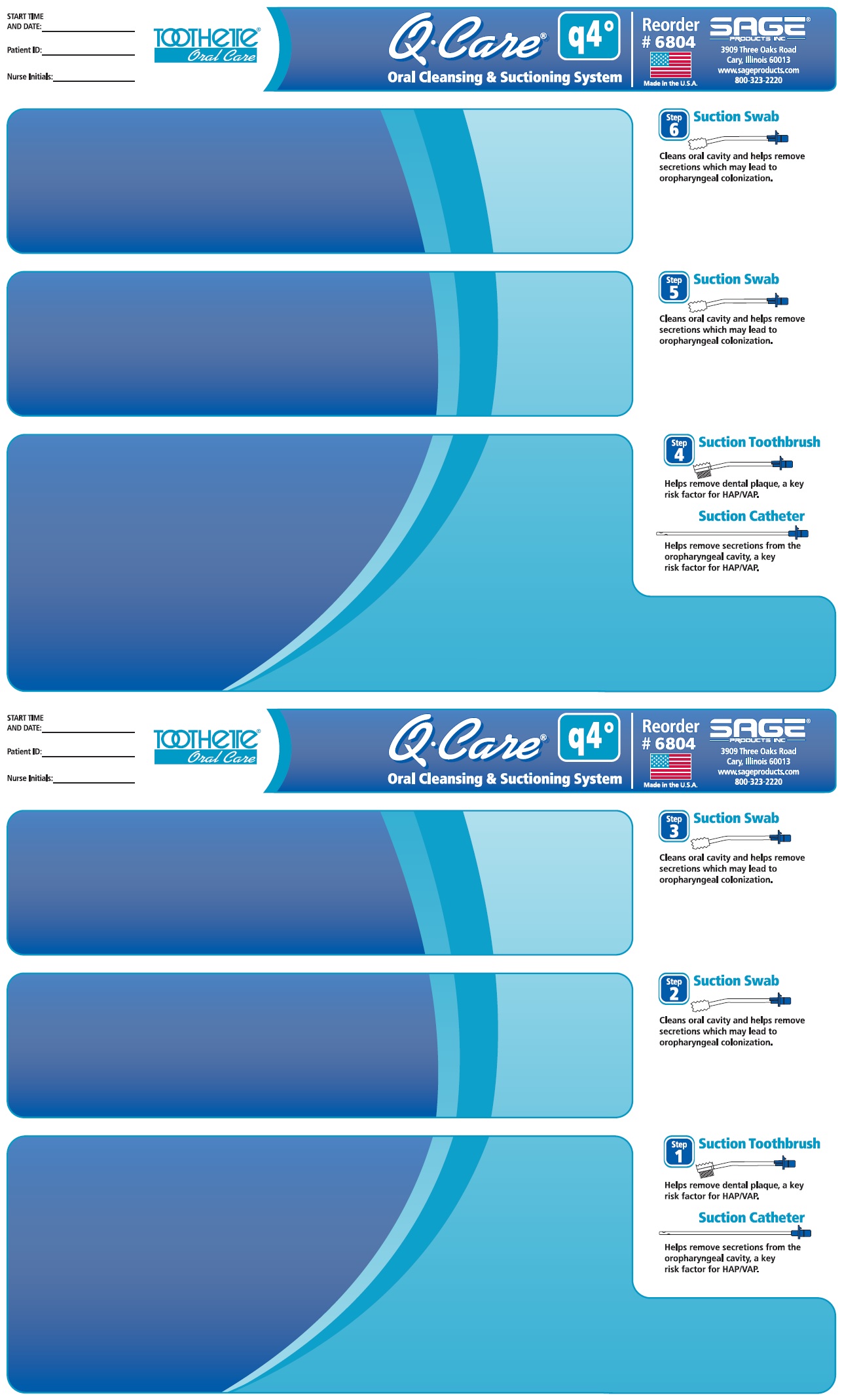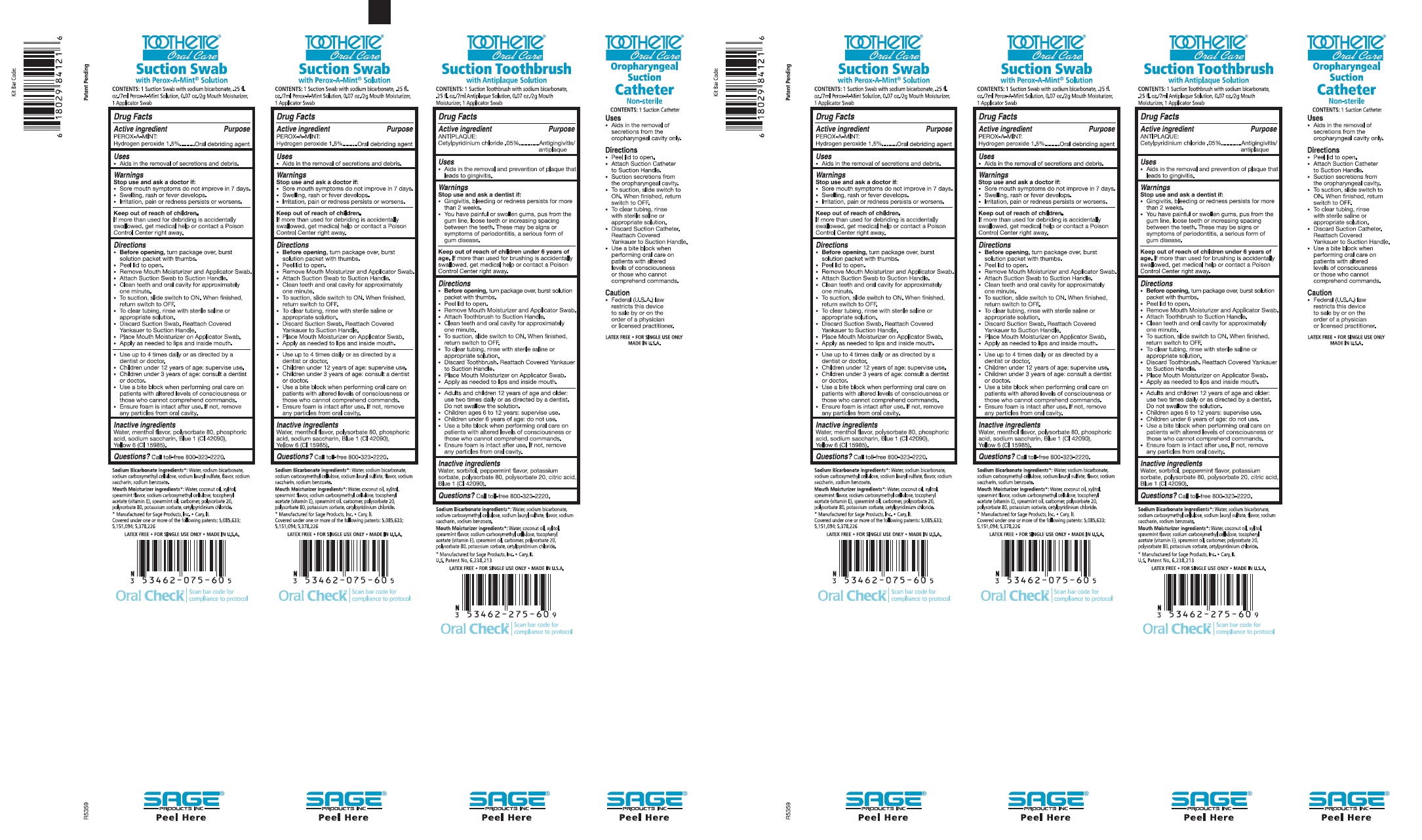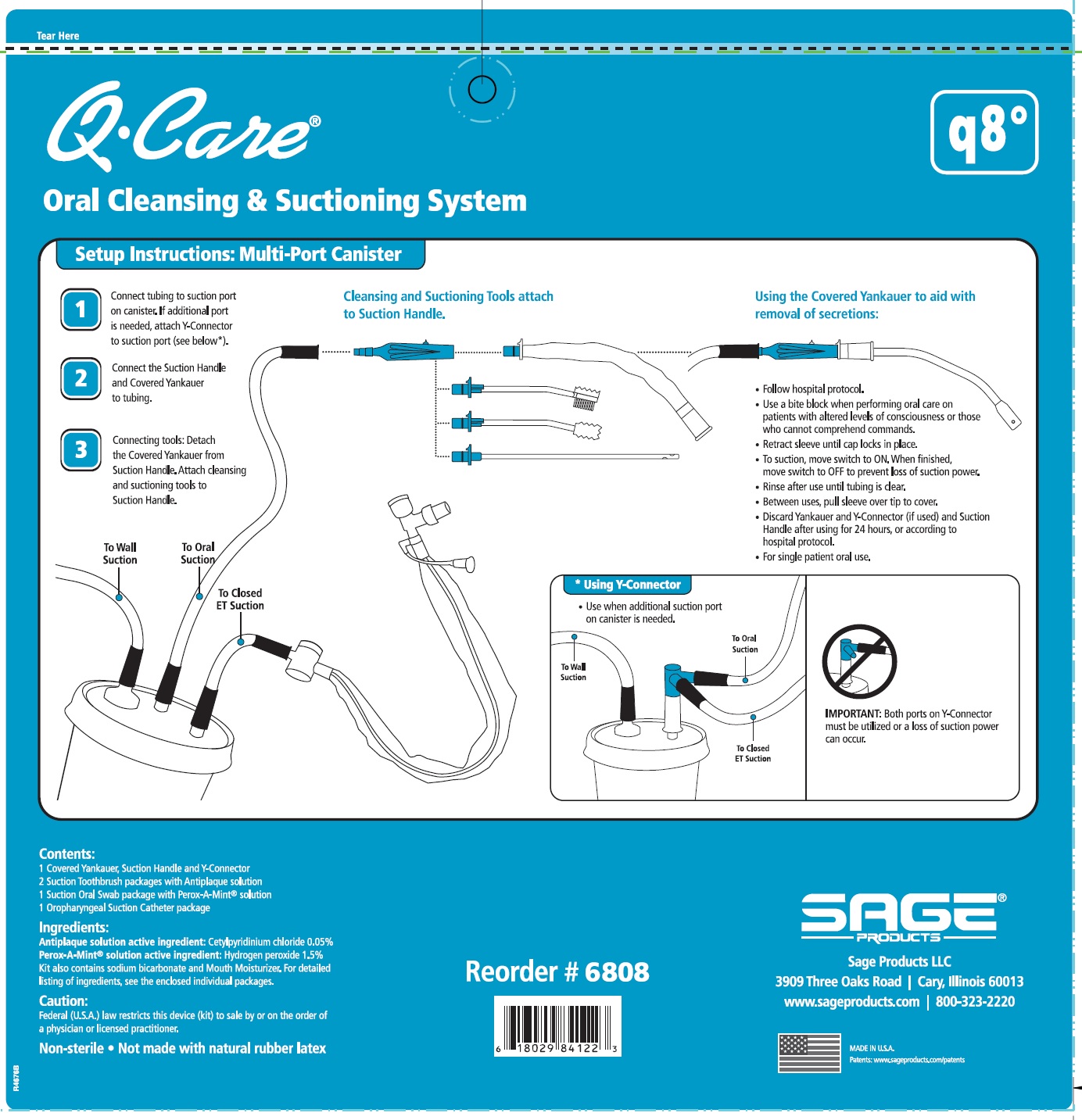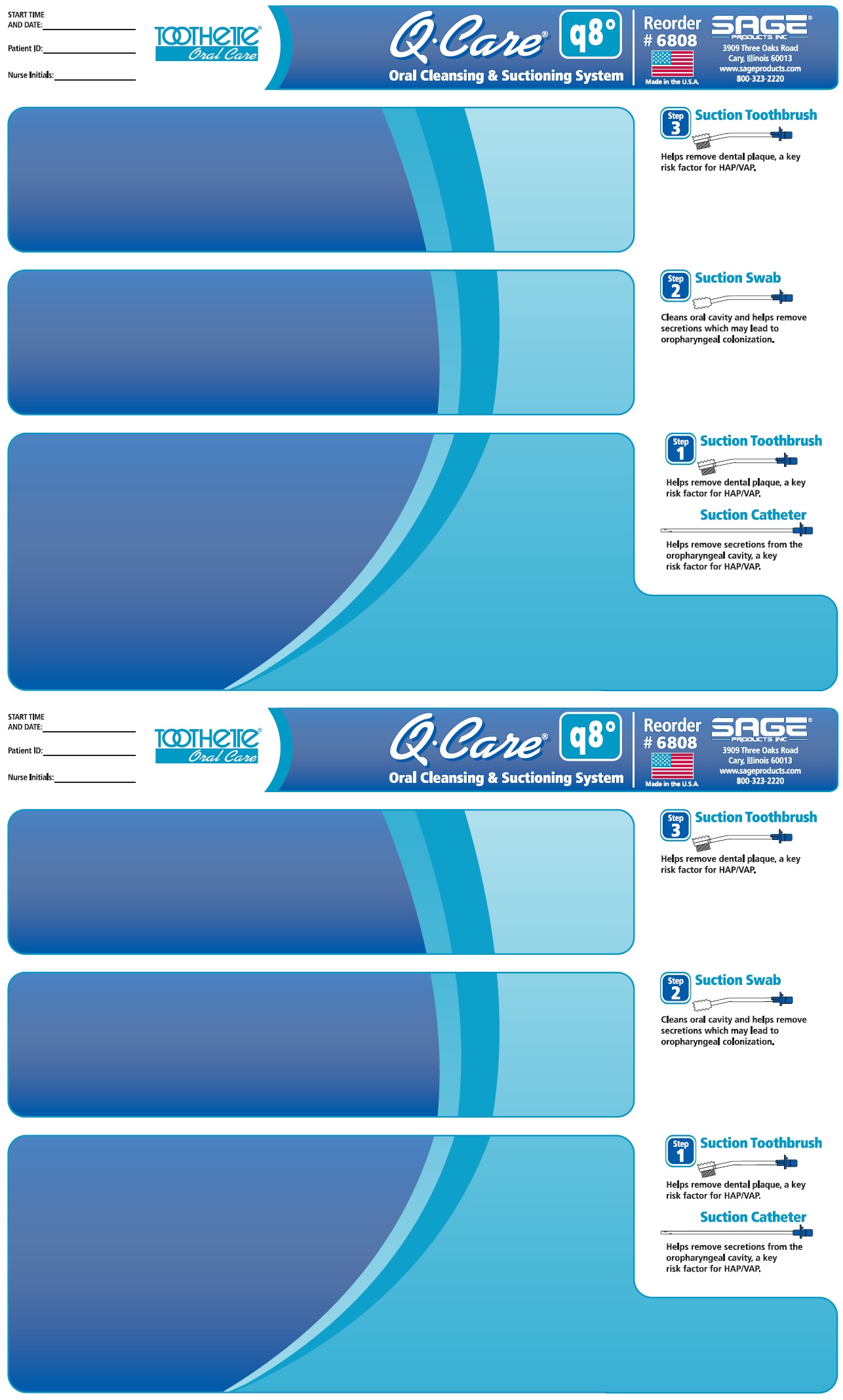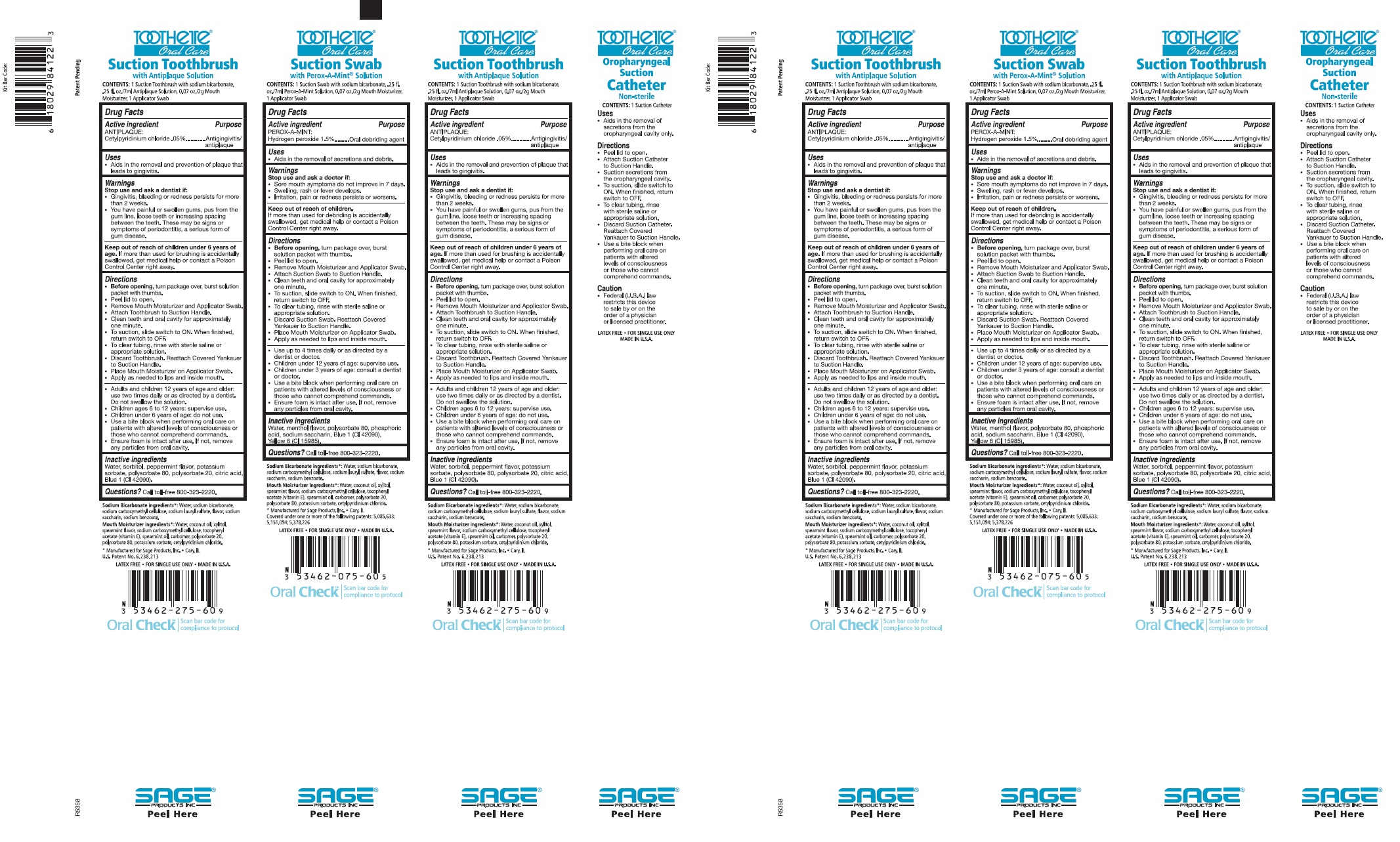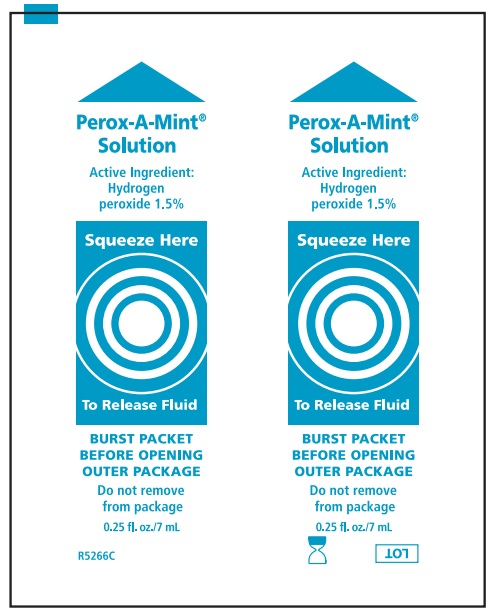 DRUG LABEL: QCare Oral Cleansing and Suctioning System, Q4
NDC: 53462-804 | Form: KIT | Route: BUCCAL
Manufacturer: Sage Products LLC
Category: otc | Type: HUMAN OTC DRUG LABEL
Date: 20220222

ACTIVE INGREDIENTS: HYDROGEN PEROXIDE 15 mg/1 mL; CETYLPYRIDINIUM CHLORIDE 0.5 mg/1 mL
INACTIVE INGREDIENTS: WATER; POLYSORBATE 80; PHOSPHORIC ACID; SACCHARIN SODIUM; FD&C BLUE NO. 1; FD&C YELLOW NO. 6; SORBITOL; POTASSIUM SORBATE; POLYSORBATE 80; POLYSORBATE 20; FD&C BLUE NO. 1; WATER; CITRIC ACID MONOHYDRATE

QCare Oral Cleansing and Suctioning System

Drug Facts

Active Ingredient: PEROX-A-MINT: | Purpose
Hydrogen Peroxide 1.5% | Oral Debriding Agent

Active Ingredient: ANTIPLAQUE*: | Purpose
Cetylpyridinium chloride .05% | Antigingivitis/antiplaque

USES

Suction Swab with Perox-A-Mint:
Aids in the removal of secretions and debris.

Suction Toothbrush with Antiplaque Solution:
Aids in the removal and prevention of plaque that leads to gingivitis.

Oropharyngeal Suction Catheter:
Aids in the removal of secretions from the oropharyngeal cavity only.

WARNINGS

Suction Swab with Perox-A-Mint Solution:

Stop use and ask a doctor if:
- Sore mouth symptoms do not improve in 7 days.
- Swelling, rash or fever develops.
- Irritation, pain or redness persists or worsens.

Suction Toothbrush with Antiplaque Solution:

Stop use and ask a dentist if:
- Gingivitis, bleeding or redness persists for more than 2 weeks.
- You have painful or swollen gums, pus from the gum line, loose teeth or increasing spacing between the teeth. These may be signs or symptoms of periodontitis, a serious form of gum disease.

KEEP OUT OF REACH OF CHILDREN

Suction Swab with Perox-A-Mint Solution:
Keep out of reach of children.
If more than used for debriding is accidentally swallowed, get medical help or contact a Poison Control Center right away.

Suction Toothbrush with Antiplaque Solution:
Keep out of reach of children under 6 years of age
If more than used for brushing is accidentally swallowed, get medical help or contact a Poison Control Center right away.

DIRECTIONS

Suction Swab with Perox-A-Mint Solution:

- Before opening, turn package over, burst solution packet with thumbs.
- Peel lid to open.
- Remove Mouth Moisturizer and Applicator Swab.
- Attach Suction Swab to Suction Handle.
- Clean teeth and oral cavity for approximately one minute.
- To suction, slide switch to ON. When finished, return switch to OFF.
- To clear tubing, rinse with sterile saline or appropriate solution.
- Discard Suction Swab. Reattach Covered Yankauer to Suction Handle.
- Place Mouth Moisturizer on Applicator Swab.
- Apply as needed to lips and inside mouth.
- Use up to 4 times daily or as directed by a dentist or doctor.
- Children under 12 years of age: supervise use.
- Children under 3 years of age: consult a dentist or doctor.
- Use a bite block when performing oral care on patients with altered levels of consciousness or those who cannot comprehend commands.
- Ensure foam is intact after use. If not, remove any particles from oral cavity.

Suction Toothbrush with Antiplaque Solution:

- Before opening, turn package over, burst solution packet with thumbs.
- Peel lid to open.
- Remove Mouth Moisturizer and Applicator Swab.
- Attach Toothbrush to Suction Handle.
- Clean teeth and oral cavity for approximately one minute.
- To suction, slide switch to ON. When finished, return switch to OFF.
- To clear tubing, rinse with sterile saline or appropriate solution.
- Discard Toothbrush. Reattach Covered Yankauer to Suction Handle.
- Place Mouth Moisturizer on Applicator Swab.
- Apply as needed to lips and inside mouth.
- Adults and children 12 years of age and older: use two times daily or as directed by a dentist. Do not swallow the solution.
- Children ages 6 to 12 years: supervise use.
- Children under 6 years of age: do not use.
- Use a bite block when performing oral care on patients with altered levels of consciousness or those who cannot comprehend commands.
- Ensure foam is intact after use. If not, remove any particles from oral cavity.

Oropharyngeal Suction Catheter:

- Peel lid to open.
- Attach Suction Cather to Suction Handle.
- Suction secretions from the oropharyngeal cavity.
- To suction, slide switch to ON. When finished, return switch to OFF.
- To clear tubing, rinse with sterile saline or appropriate solution.
- Discard Suction Catheter. Reattach Covered Yankauer to Suction Handle.
- Use a bite block when performing oral care on patients with altered levels of consciousness or those who cannot comprehend commands.

Caution

- Federal (U.S.A.) law restricts this device to sale by or on the order of a physician or licensed practicioner.

Inactive Ingredients

Suction Swab with Perox-A-Mint Solution:

Water, menthol flavor, polysorbate 80, phosphoric acid, sodium saccharin, Blue 1 (CI 42090), Yellow 6 (CI 15985)

Suction Toothbrush with Antiplaque Solution:

Water, sorbitol, peppermint flavor, potassium sorbate, polysorbate 80, polysorbate 20, citric acid, Blue 1 (CI42090)

Questions?

Call toll-free 800–323–2220

Manufactured for Sage Products LLC Cary, IL

NOT MADE WITH NATURAL RUBBER LATEX. FOR SINGLE USE ONLY. MADE IN U.S.A.